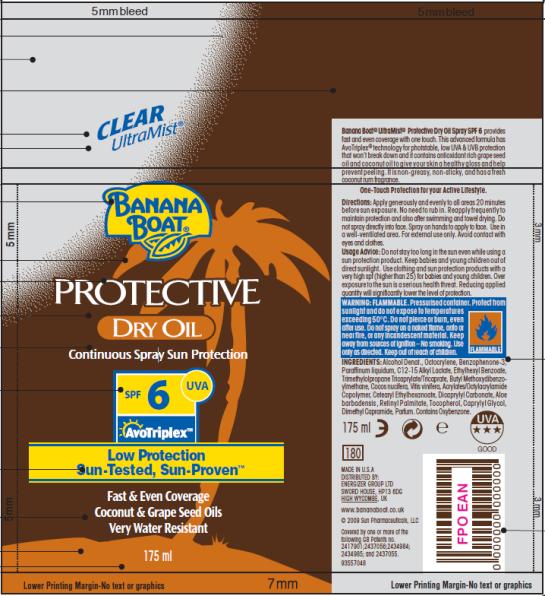 DRUG LABEL: Banana Boat Protective Dry SPF 6
NDC: 17630-2026 | Form: OIL
Manufacturer: Accra-Pac, Inc.
Category: otc | Type: HUMAN OTC DRUG LABEL
Date: 20100327

ACTIVE INGREDIENTS: OCTOCRYLENE 0.03 mL/1 mL; OXYBENZONE 0.03 mL/1 mL; AVOBENZONE 0.01 mL/1 mL
INACTIVE INGREDIENTS: MINERAL OIL; DICAPRYLYL CARBONATE; ALOE VERA LEAF; VITAMIN A PALMITATE; CAPRYLYL GLYCOL; GRAPE SEED OIL; COCONUT OIL

Banana Boat Protective Dry Oil SPF 6

Active Ingredients

Octocrylene 0.03mL / 1mL

Oxybenzone 0.03mL / 1mL

Avobenzone 0.01mL / 1mL

Directions:

Apply generously and evenly to all areas 20 minutes before sun exposure. No need to rub in. Reapply frequently to maintain protection and also after swimming and towel drying. Do not spray directly into face. Spray on hands to apply to face. Use in a well-ventilated area. For external use only. Avoid contact with eyes and clothes.

Usage Advice:

Do not stay too long in the sun even while using a sun protection product. Keep babies and young children out of direct sunlight. Use clothing and sun protection products with a very high spf (higher than 25) for babies and young children. Over exposure to the sun is a serious health threat. Reducing applied quantity will significantly lower the level of protection.

WARNING:

FLAMMABLE. Pressurized container. Protect from sunlight and do not expose to temperatures exceeding 50ºC. Do not pierce or burn, even after use. Do not spray on a naked flame, onto or near fire, or any incandescent material. Keep away from sources of ignition – No smoking. Use only as directed.

INGREDIENTS:

Alcohol Denat., Octocrylene, Benzophenone-3, Paraffinum liquidum, C12-15 Alkyl Lactate, Ethylhexyl Benzoate, Trimethylolpropane Tricaprylate/Tricaprate, Butyl Methoxydibenzoylmethane, Cocos nucifera, Vitis vinifera, Acrylates/Octylacrylamide Copolymer, Cetearyl Ethylhexanoate, Dicaprylyl Carbonate, Aloe Barbadensis leaf , Retinyl Palmitate, Tocopherol, Caprylyl Glycol, Dimethyl Capramide, Parfum. Contains Oxybenzone.

MADE IN U.S.A
DISTRIBUTED BY:
ENERGIZER GROUP LTD
SWORD HOUSE, HP13 6DG
HIGH WYCOMBE, UK
www.bananaboat.co.uk

PRINCIPAL DISPLAY PANEL

CLEAR
UltraMist®
BANANA
BOAT®
PROTECTIVE
DRY OIL
Continuous Spray Sun Protection
SPF 6 UVA
AvoTriplex TM
Low Protection
Sun-Tested, Sun-Proven TM
Fast & Even Coverage
Coconut & Grape Seed Oils
Very Water Resistant
175 ml